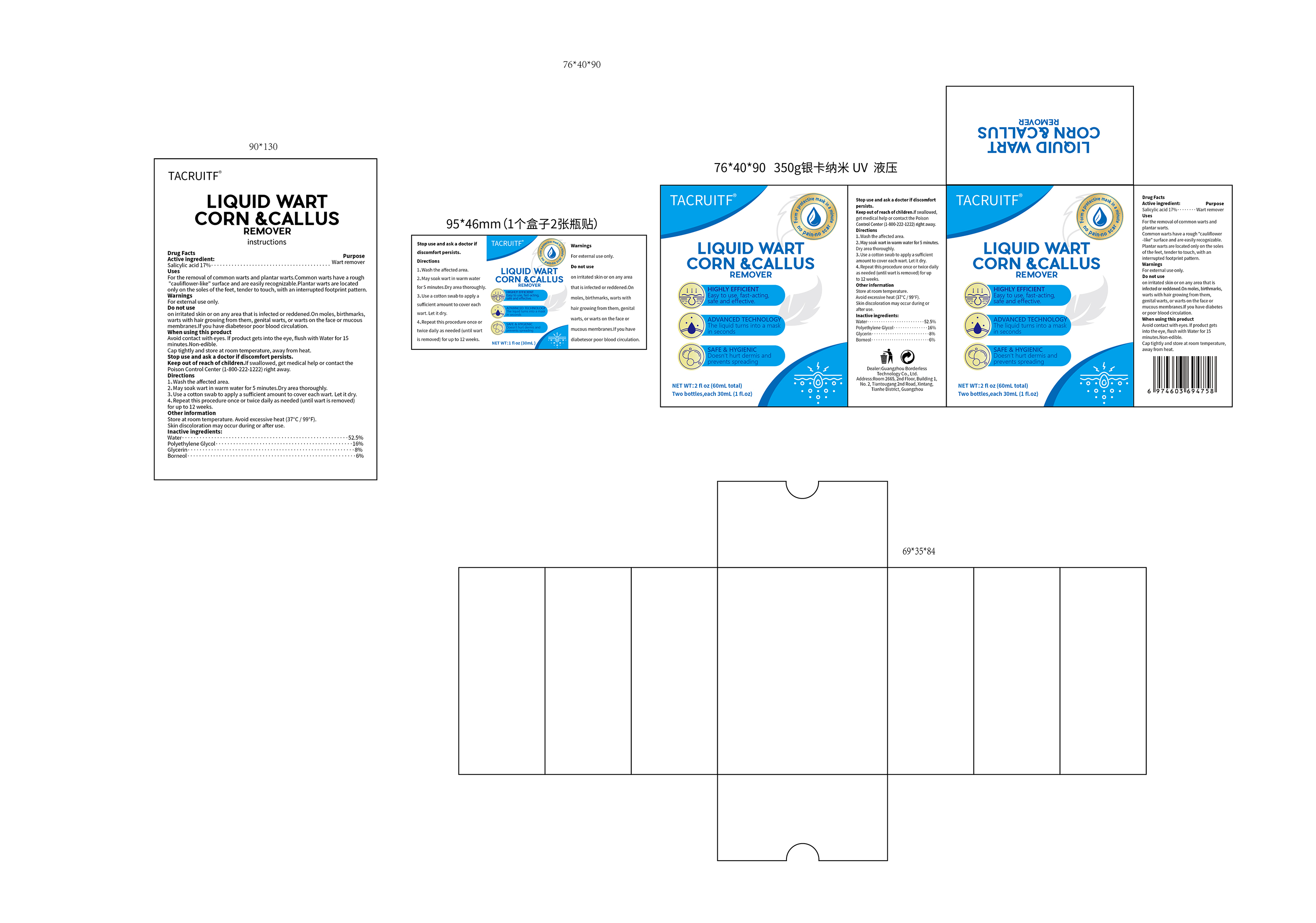 DRUG LABEL: TACRUITF 17% Salicylic acid Wart Remover Serum
NDC: 85304-010 | Form: LIQUID
Manufacturer: Guangzhou Borderless Technology Co., Ltd.
Category: otc | Type: HUMAN OTC DRUG LABEL
Date: 20250723

ACTIVE INGREDIENTS: SALICYLIC ACID 17 g/100 mL
INACTIVE INGREDIENTS: WATER; BORNEOL; POLYETHYLENE GLYCOL, UNSPECIFIED; GLYCERIN

85304-010 TACRUITF 17% Salicylic acid Wart Remover Serum

ACTIVE INGREDIENT

Salicylic acid 17%

PURPOSE

Wart remover

INDICATIONS AND USAGE

For the removal of common warts and plantar warts.Common warts have a rough"cauliflower-like" surface and are easily recognizable.Plantar warts are located only on the soles of the feet, tender to touch, with an interrupted footprint pattern.

WARNINGS

For external use only.

DO NOT USE

on irritated skin or on any area that is infected or reddened.On moles, birthmarkswarts with hair growing from them, genital warts, or warts on the face or mucousmembranes.lf you have diabetesor poor blood circulation.

WHEN USING

Avoid contact with eyes. lf product gets into the eye, flush with Water for 15
minutes.Non-edible.
Cap tightly and store at room temperature, away from heat.

DOSAGE AND ADMINISTRATION

1、Wash the affected area.

2、May soak wart in warm water for 5 minutes.Dry area thoroughly.

3、 Use a cotton swab to apply a sufficient amount to cover each wart. Let it dry

4、 Repeat this procedure once or twice daily as needed (until wart is removed)for up to 12 weeks.

INACTIVE INGREDIENT

Water
Polyethylene Glycol
Glycerin
Borneol